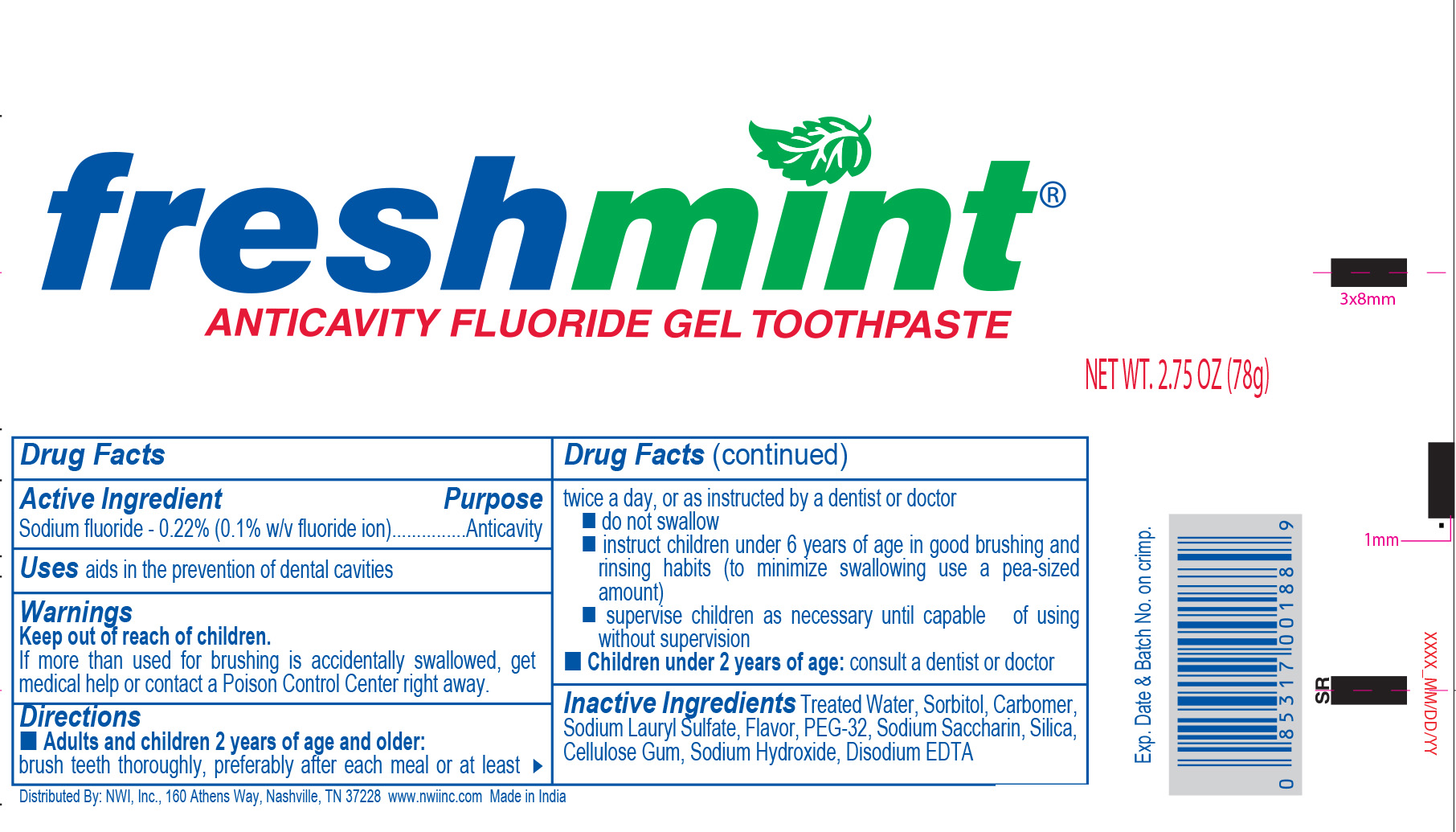 DRUG LABEL: Freshmint Anticavity Fluoride
NDC: 51824-068 | Form: GEL, DENTIFRICE
Manufacturer: New World Imports, Inc
Category: otc | Type: HUMAN OTC DRUG LABEL
Date: 20250115

ACTIVE INGREDIENTS: Sodium Fluoride 2.2 mg/1 g
INACTIVE INGREDIENTS: Water; Sorbitol; CARBOMER HOMOPOLYMER TYPE C; Sodium Lauryl Sulfate; POLYETHYLENE GLYCOL 1600; Saccharin Sodium; Silicon Dioxide; Carboxymethylcellulose Sodium; SODIUM HYDROXIDE; EDETATE DISODIUM ANHYDROUS

Drug Facts

ACTIVE INGREDIENT

Sodium Fluoride - 0.22% (0.1% w/v fluoride ion)

PURPOSE

Anticavity

Keep out of reach of children. If more than used for brushing is accidentally swallowed, get medical help or contact a Poison Control Center right away.

INDICATIONS AND USAGE

aids in the prevention of dental cavities

Keep out of reach of children. If more than used for brushing is accidentally swallowed, get medical help or contact a Poison Control Center right away.

DOSAGE AND ADMINISTRATION

Adults and children 2 years of age and older: Brush teeth thoroughly, preferably after each meal or at least twice a day, or as directed by a dentist or physician.

- do not swallow
- instruct children under 6 years of age in good brushing and rinsing habits (to minimize swallowing use a pea-sized amount)
- supervise children as necessary until capable of using without supervision

Children under 2 years: Ask a dentist or doctor

INACTIVE INGREDIENT

Treated Water, Sorbitol, Carbomer, Sodium Lauryl Sulfate, Flavor, PEG-32, Sodium Saccharin, Silica, Cellulose Gum, Sodium Hydroxide, Disodium EDTA